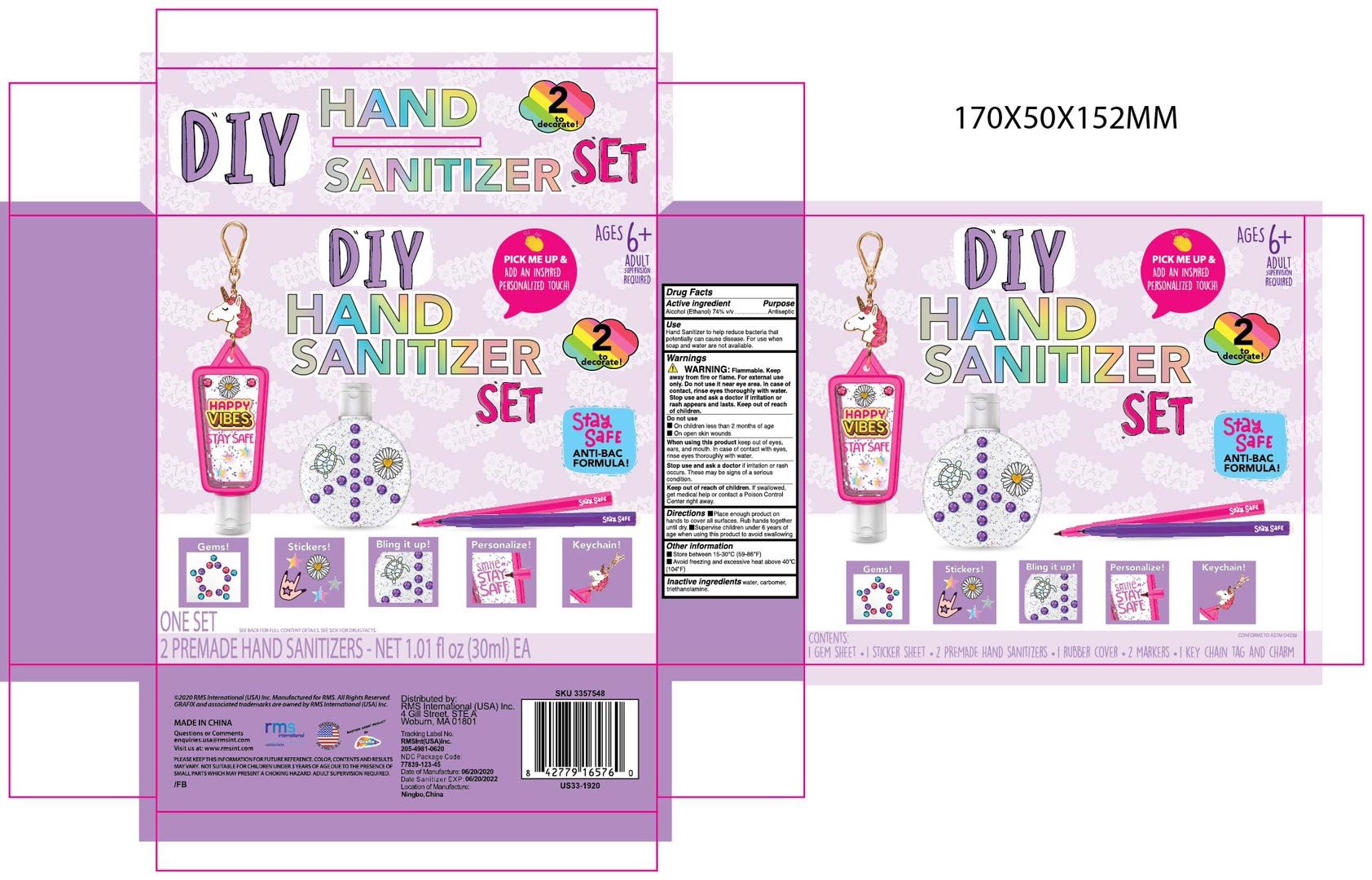 DRUG LABEL: Hand Sanitizer
NDC: 77839-123 | Form: LIQUID
Manufacturer: RMS International (USA) Inc.
Category: otc | Type: HUMAN OTC DRUG LABEL
Date: 20200708

ACTIVE INGREDIENTS: ALCOHOL 74 mL/100 mL
INACTIVE INGREDIENTS: CARBOMER HOMOPOLYMER, UNSPECIFIED TYPE 0.2 mL/100 mL; TROLAMINE 0.15 mL/100 mL; WATER

DIY Hand Sanitizer Set

This is a hand sanitizer is manufactured in accordance with the applicable topical anti-microbial OTC Monograph (Not Final).

Active Ingredient(s)

Alcohol 74% v/v

Purpose: Antiseptic

Purpose

Antiseptic, Hand Sanitizer

Use

Hand Sanitizer to help reduce bacteria that potentially can cause disease. For use when soap and water are not available.

Warnings

WARNING: Flammable. Keep away from fire or flame. For external use only. Do not use it near eye area. In case of contact, rinse eyes thouroughly with water. Stop use and ask doctor if irritation or rash appears and lasts. Keep out of the reach of children.

Do not use

On children less than 2 months of age.

On open skin wounds.

When using this product keep out of eyes, ears, and mouth. In case of contact with eyes, rinse eyes thoroughly with water.

Stop use and ask a doctor if irritation or rash occurs. These may be signs of a serious condition.

Keep out of reach of children. If swallowed, get medical help or contact a Poison Control Center right away.

Directions

- Place enough product on hands to cover all surfaces. Rub hands together until dry.
- Supervise children under 6 years of age when using this product to avoid swallowing.

Other information

- Store between 15-30C (59-86F)
- Avoid freezing and excessive heat above 40C (104F)

Inactive ingredients

Water, Carbomer, triethanolamine

Package Label - Principal Display Panel

PDP